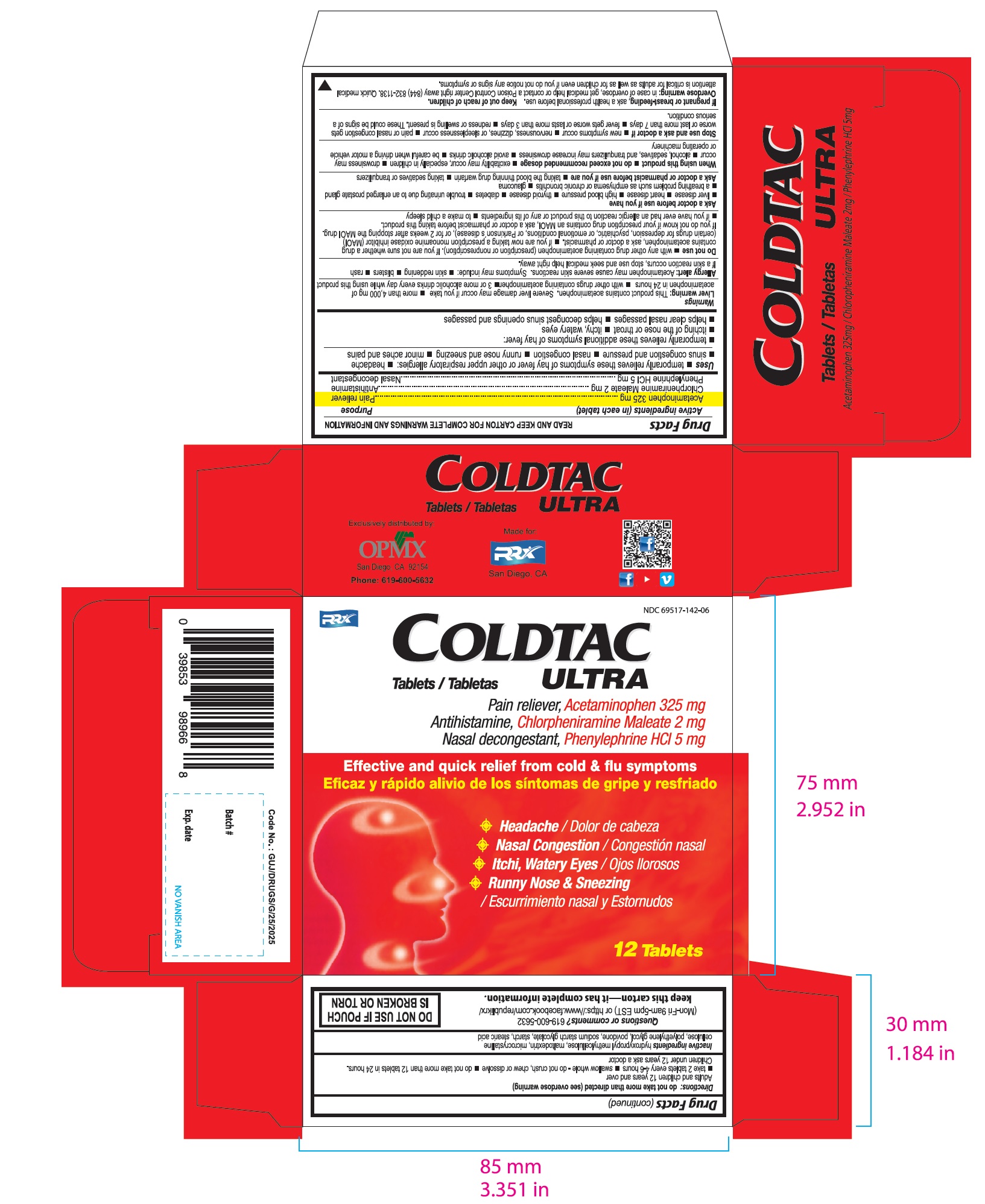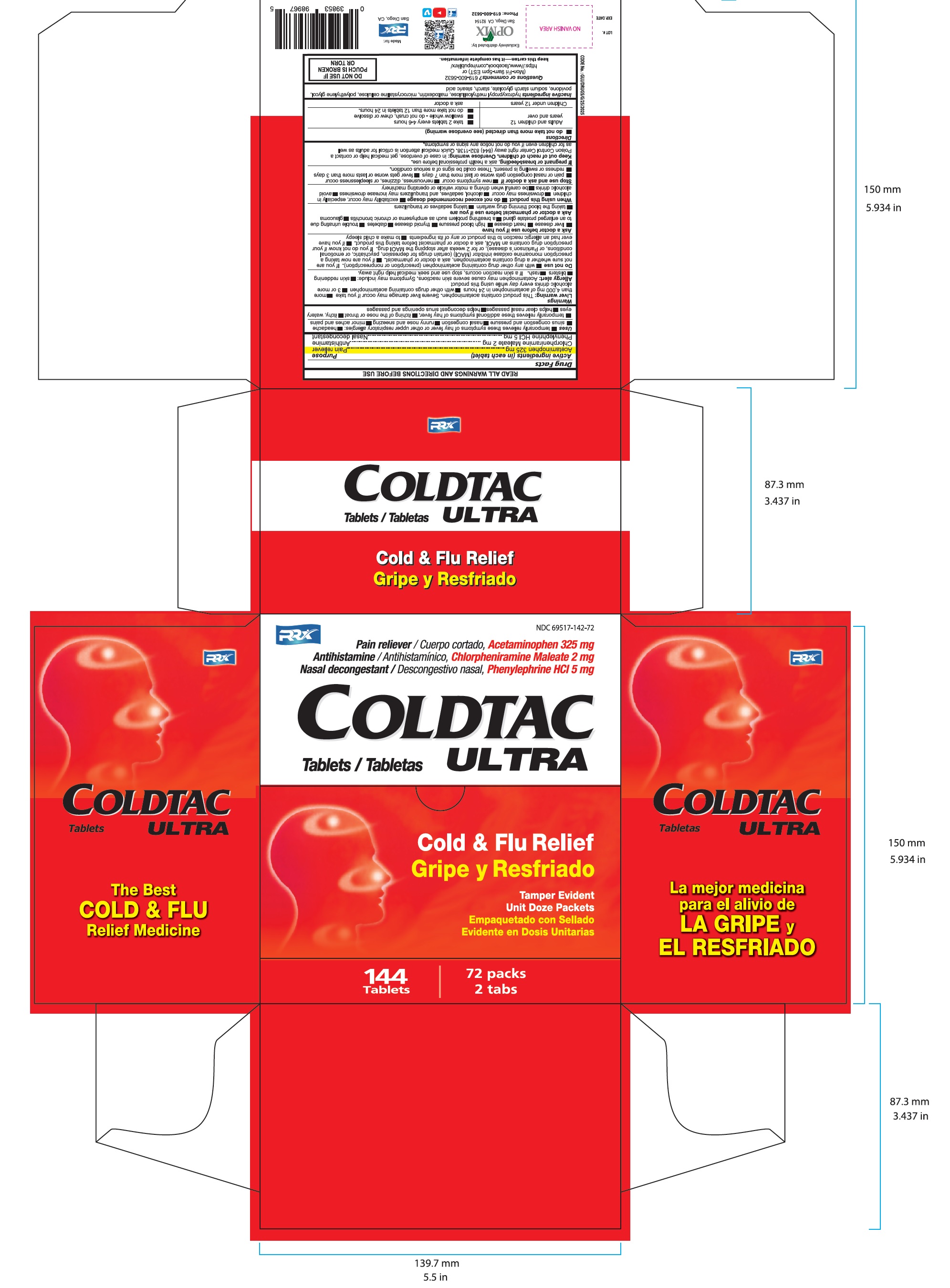 DRUG LABEL: COLDTAC ULTRA
NDC: 69729-142 | Form: TABLET
Manufacturer: OPMX LLC
Category: otc | Type: HUMAN OTC DRUG LABEL
Date: 20180105

ACTIVE INGREDIENTS: ACETAMINOPHEN 325 mg/1 1; CHLORPHENIRAMINE MALEATE 2 mg/1 1; PHENYLEPHRINE HYDROCHLORIDE 5 1/1 1
INACTIVE INGREDIENTS: HYPROMELLOSE, UNSPECIFIED; SODIUM STARCH GLYCOLATE TYPE A CORN; POLYETHYLENE GLYCOL, UNSPECIFIED; MALTODEXTRIN; CELLULOSE, MICROCRYSTALLINE; STEARIC ACID; STARCH, CORN; POVIDONE

COLDTAC ULTRA

DRUG FACTS

ACTIVE INGREDIENTS:

Acetaminophen USP 325mg........................................Pain reliever
Chlorpheniramine Maleate USP 2mg.............................Antihistamine
Phenylephrine HCL USP 5mg.......................................Nasal decongestant

Purpose

Pain reliever

Antihistamine

Nasal decongestant

USES

Tempporarily relieves these symptoms of hay fever or other upper respiratory allergies:

- headache
- sinus congestion and pressure
- nasal congestion
- runny nose and sneezing
- minor aches and pains

Temporarily relieves these additional symptoms of hay fever:

- itching of the nose or throat
- itchy, watery eyes
- helps clear nasal passages
- helps decongest sinus openings and passages

WARNINGS

Liver warning:

This product contains acetaminophen. Severe liver damage may occur if you take

- more than 4,000 mg of acetaminophen in 24 hours
- with other drugs containing acetaminophen
- 3 or more alcoholic drinks every day while using this product

ALLERGY ALERT

Acetaminophen may cause severe skin reactions. Symptoms may include:

- skin reddening
- blisters
- rash if a skin reaction occurs, stop use and seek medical help right away

Do not use

- with any other drug containing acetaminophen (prescription or nonprescription). if you are not sure whether a drug contains acetaminophen, ask a doctor or pharmacist.
- if you are now taking a prescription monoamine oxidase inhibitor (MAOI) (certain dugs for depression, psychiatric, or emotional conditions, or Parkinson's disease), or for 2 weeks after stopping the MAOI drug. If you do not know if your prescription drug contains a MAOI, ask a doctor or pharmacist before taking this product.
- if you have ever had an allergic reaction to this product or any of its ingredients
- to make a child sleepy

Ask a doctor before use if you have

liver disease, heart disease, high blood pressure, thyroid disease, diabetes, trouble urinating due to an enlarged prostate gland, a breathing problem such as emphysema or chronic bronchitis, glaucoma

Ask a doctor or pharmacist before use if you are

- taking the blood thinning drug warfarin
- taking sedatives or tranquilizers

When using this product

- do not exceed recommended dosage
- excitability may occur, especially in children
- drowsiness may occur
- alcohol, sedatives, and tranquilizers may increase drowsiness
- avoid alcoholic drinks
- be careful when driving a motor vehicle or operating machinery

Stop use and ask a doctor if

- new symptoms occur
- nervousness, dizziness, or sleeplessness occur
- pain or nasal congestion gets worse or last more than 7 days
- fever gets worse or lasts more than 3 days
- redness or swelling is present.
- These could be signs of a serious condition.

If pregnant or breast-feeding,

ask a health professional before use.

Overdose warning

in case of overdose, get medical help or contact a Poison Control Center right away (844) 832-1138. Quick medical attention is critical for adults as well as for children even if you do not notice any signs or symptoms.

Directions: do not take more than directed (see overdose warning)

Adults and children 12 years and over:

- take 2 tablets every 4-6 hours
- swallow whole - do not crush, chew or dissolve
- do not take more than 12 tablets in 24 hours

Children under 12 years: ask a doctor

OTHER INFORMATION

- Tamper evident. do not use if packet is torn, cut or opened
- Store at controlled room temperature 15° to 30°C (59° to 86°F)
- Avoid excessive heat and humidity

Inactive Ingredients

hydroxypropyl methylcellulose, methylcellulose, maltodextrin, microcrystalline cellulose, polyethylene glycol, povidone, sodium starch glycolate, starch, stearic acid

Questions or comments? 619-600-5632

(Mon-Fri 9am - 5pm EST) or https://www/facebook.com/republikrx/

The carton has the complete information.